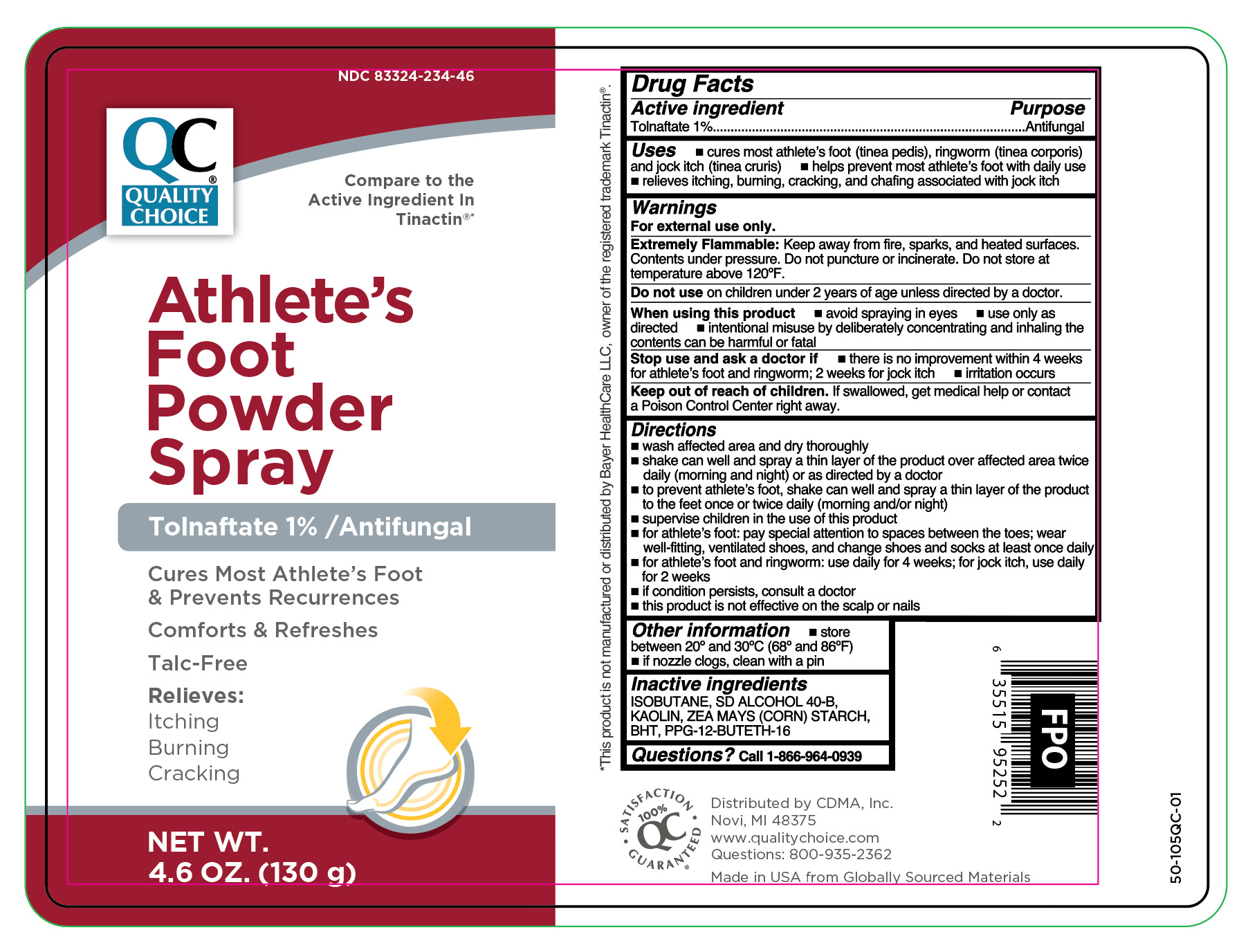 DRUG LABEL: Tolnafate
NDC: 83324-234 | Form: AEROSOL, SPRAY
Manufacturer: Chain Drug Marketing Association
Category: otc | Type: HUMAN OTC DRUG LABEL
Date: 20251106

ACTIVE INGREDIENTS: TOLNAFTATE 10 mg/1 g
INACTIVE INGREDIENTS: ZEA MAYS (CORN) STARCH; BHT; PPG-12-BUTETH-16; ISOBUTANE; KAOLIN; ALCOHOL

Quality Choice Tolnaftate Powder Spray Talc-Free

Active ingredient

Tolnaftate 1%

Purpose

Antifungal

Uses

- cures most athlete's foot (tinea pedis), ringworm (tinea corporis) and jock itch (tinea cruris)
- helps prevent most athlete's foot with daily use
- relieves itching, burning, cracking, and chafing associated with jock itch

WARNINGS

For external use only.

Extremely Flammable:

Keep away from fire, sparks, and heated surfaces.

Contents under pressure.Do not puncture or incinerate. Do not store at

temperature above 120ºF.

Do not use

on children under 2 years of age unless directed by a doctor.

When using this product

- avoid spraying in eyes
- use only as directed
- intentional misuse by deliberately concentrating and inhaling the contents can be harmful or fatal.

Stop use and ask a doctor if

- there is no improvement within 4 weeks for athlete's foot and ringworm; 2 weeks for jock itch
- irriration occurs

Keep out of reach of children.

If swallowed, get medical help or contact a Poison Control Center right away.

Directions

- wash affected area and dry thoroughly
- shake can well and spray a thin layer of the product over affected area twice daily (morning and night) or as directed by a doctor
- to prevent athlete's foot, shake can well and spray a thin layer of the product to the feet once or twice daily (morning and/or night)
- supervise children in the use of this product
- for athlete's foot: pay special attention to spaces between the toes; wear well-fitting, ventilated shoes, and change shoes and socks at least once daily
- for athlete's foot and ringworm: use daily for 4 weeks; for jock itch, use daily for 2 weeks
- if condition persists, consult a doctor
- this product is not effective on the scalp or nails

Other information

- store between 20º and 30ºC (68º and 86ºF)
- if nozzle clogs, clean with a pin

Inactive ingredients

Isobutane, SD Alcohol 40-B, Kaolin, Zea Mays (Corn) Starch,BHT, PPG-12-Buteth-16

Questions?

call 1-866-964-0939

RECENT MAJOR CHANGES

.

Principal Display Panel

QC Quality Choice

Athlete's

Foot

Powder

Spray

Tolnaftate 1% / Antifungal

Cures Most Athlete's Foot

& Prevents Recurrences

Comforts & Refreshes

Talc-Free

Relieves:

Itching

Burning

Cracking

NET WT.

4.6 OZ. (130 g)